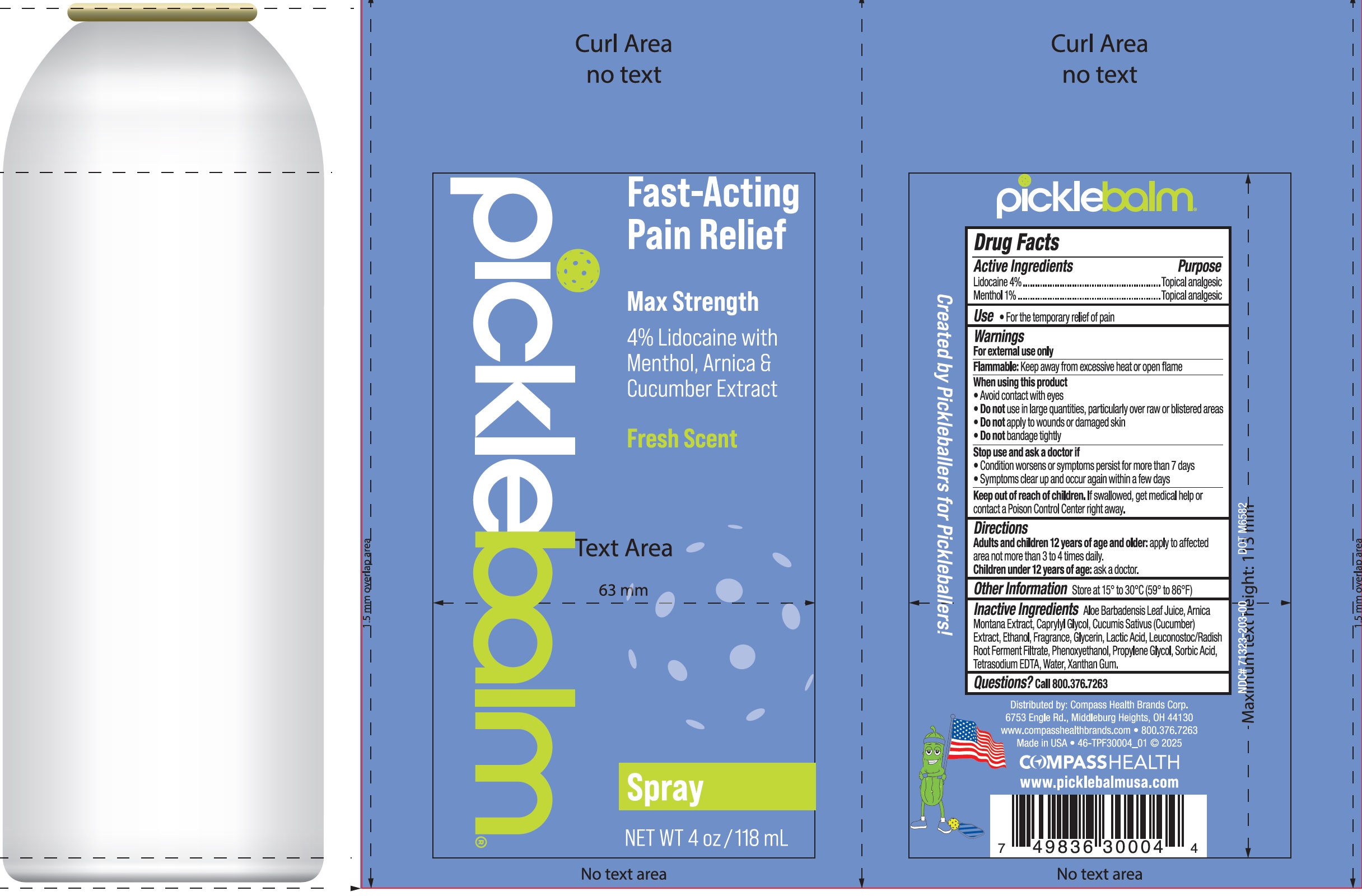 DRUG LABEL: PICKLEBALM LIDOCAINE WITH MENTHOL ARNICA CUCUMBER SEED
NDC: 71323-203 | Form: LIQUID
Manufacturer: Compass Health Brands Corp.
Category: otc | Type: HUMAN OTC DRUG LABEL
Date: 20250422

ACTIVE INGREDIENTS: LIDOCAINE 40 mg/1 mL; MENTHOL, UNSPECIFIED FORM 10 mg/1 mL
INACTIVE INGREDIENTS: ALOE VERA LEAF JUICE; ARNICA MONTANA WHOLE; CAPRYLYL GLYCOL; CUCUMBER; ALCOHOL; GLYCERIN; LACTIC ACID, UNSPECIFIED FORM; LEUCONOSTOC/RADISH ROOT FERMENT FILTRATE; PHENOXYETHANOL; PROPYLENE GLYCOL; SORBIC ACID; EDETATE SODIUM; WATER; XANTHAN GUM

PICKLEBALM LIDOCAINE WITH MENTHOL ARNICA CUCUMBER SEED SPRAY

Active Ingredients

Lidocaine 4%

Menthol 1%

Purpose

Topical analgesic

Use

- For the temporary relief of pain

Warnings

For external use only

Flammable:Keep away from excessive heat or open flame

When using this product

- Avoid contact with eyes
- Do notuse in large quantities, particularly over raw or blistered areas
- Do notapply to wounds or damaged skin
- Do notbandage tightly

Stop use and ask a doctor if

- Condition worsens or symptoms persist for more than 7 days
- Symptoms clear up and occur again within a few days

Keep out of reach of children.

If swallowed, get medical help or contact a Poison Control Center right away.

Directions

Adults and children 12 years of age and older:apply to affected area not more than 3 to 4 times daily.

Children under 12 years of age: ask a doctor.

Other Information

- Store at 15° to 30°C (59° to 86°F)

Inactive Ingredients

Aloe Barbadensis Leaf Juice, Arnica Montana Extract, Caprylyl Glycol, Cucumis Sativa (Cucumber) Extract, Ethanol, Fragrance, Glycerin, Lactic Acid, Leuconostoc/Radish Root Ferment Filtrate, Phenoxyethanol, Propylene Glycol, Sorbic Acid, Tetrasodium EDTA, Water, Xanthan Gum.

Questions?

Call 800.376.7263